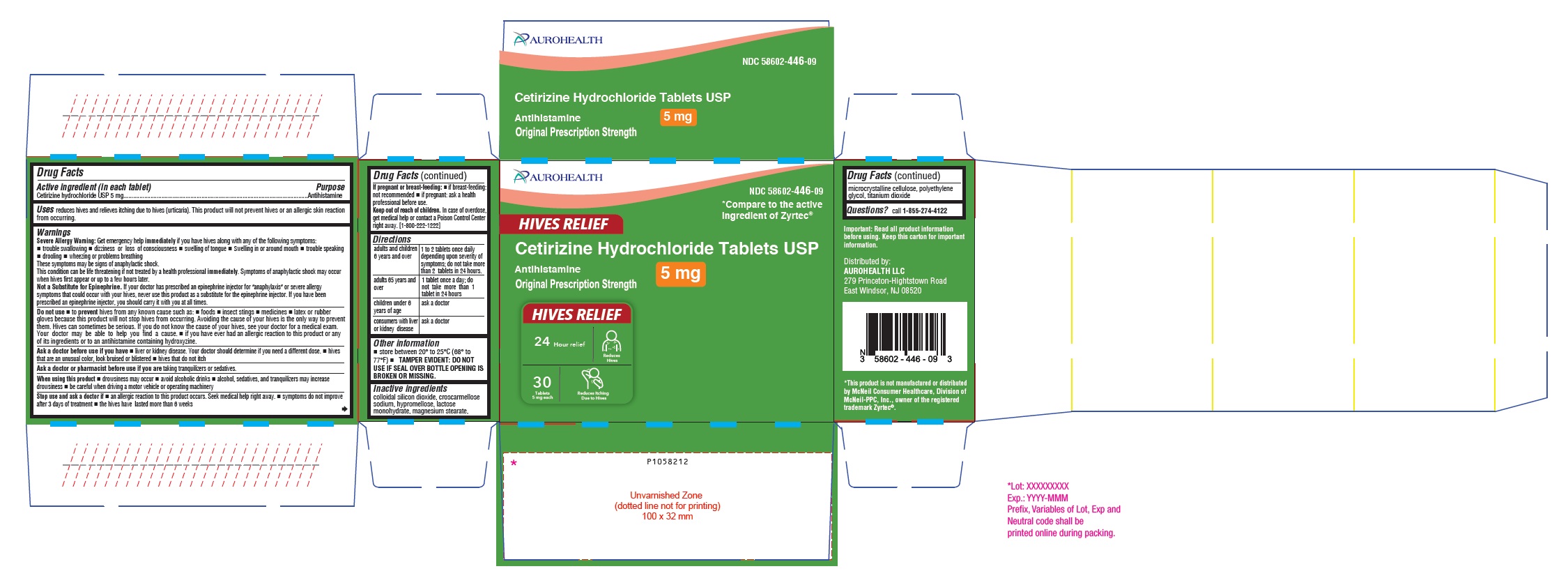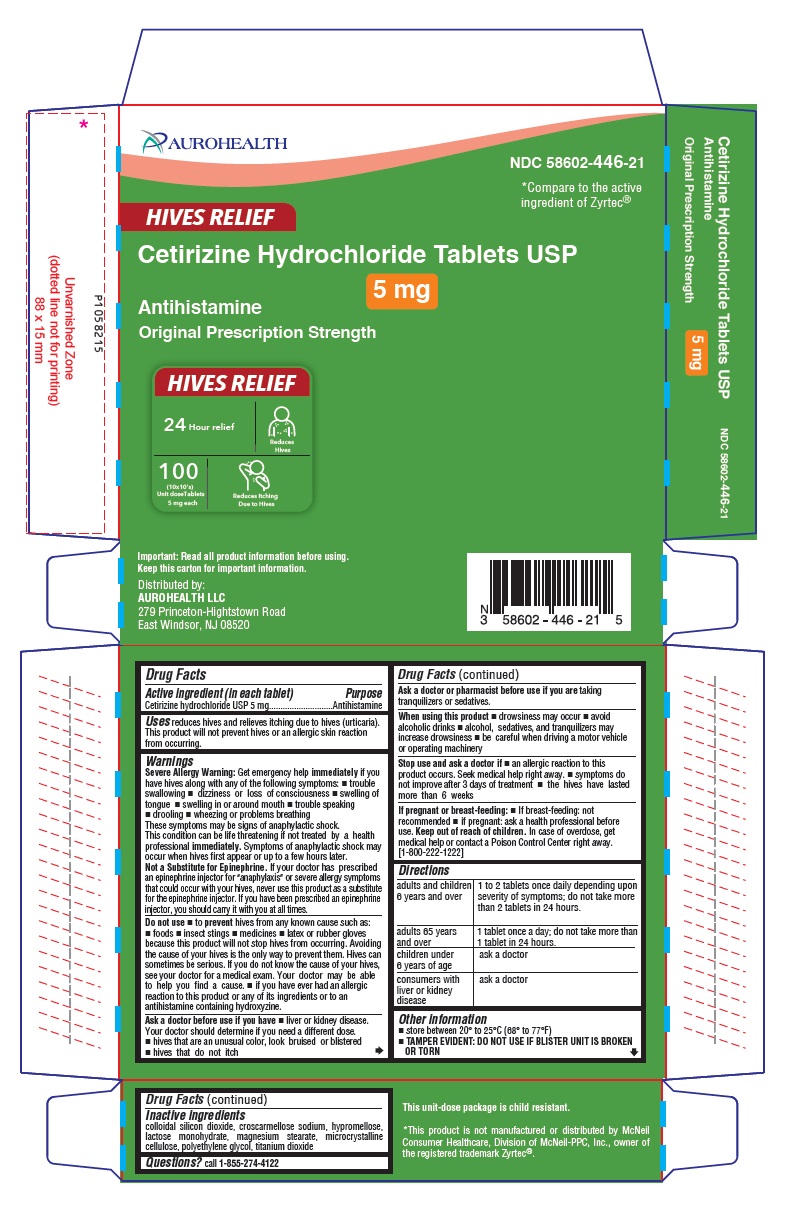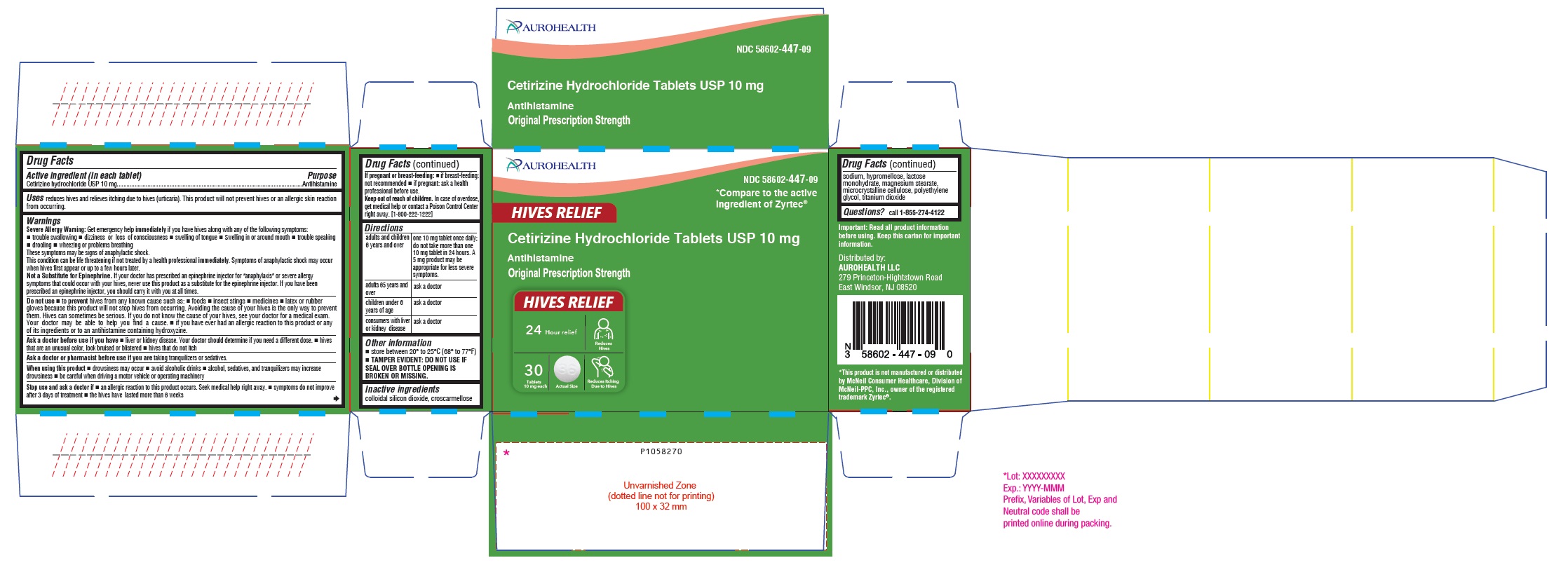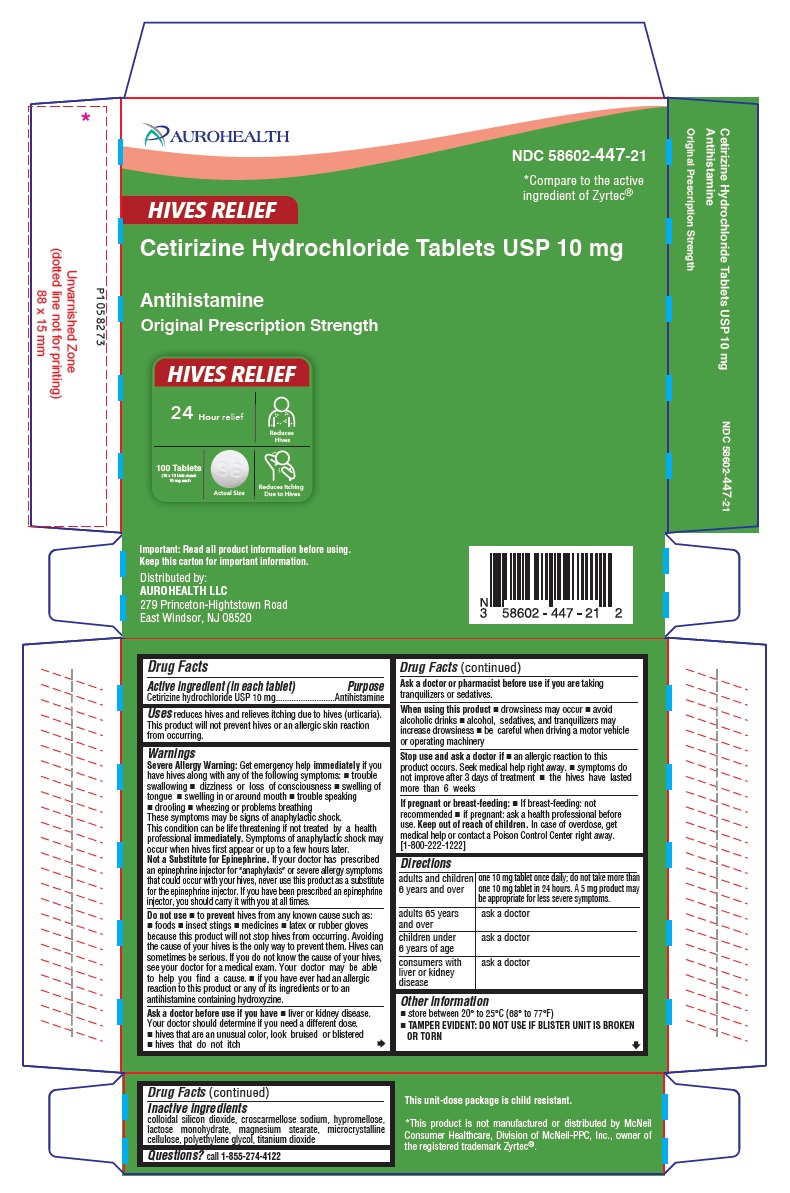 DRUG LABEL: Cetirizine Hydrochloride (Hives Relief)
NDC: 58602-446 | Form: TABLET
Manufacturer: Aurohealth LLC
Category: otc | Type: Human OTC Drug Label
Date: 20250210

ACTIVE INGREDIENTS: CETIRIZINE HYDROCHLORIDE 5 mg/1 1
INACTIVE INGREDIENTS: SILICON DIOXIDE; CROSCARMELLOSE SODIUM; HYPROMELLOSE 2910 (5 MPA.S); LACTOSE MONOHYDRATE; MAGNESIUM STEARATE; CELLULOSE, MICROCRYSTALLINE; POLYETHYLENE GLYCOL 400; TITANIUM DIOXIDE

Drug Facts

Active ingredient (in each tablet)

For 5 mg:
Cetirizine hydrochloride USP 5 mg
For 10 mg:
Cetirizine hydrochloride USP 10 mg

Purpose

Antihistamine

Uses

reduces hives and relieves itching due to hives (urticaria). This product will not prevent hives or an allergic skin reaction from occurring.

Warnings

Severe Allergy Warning: Get emergency help immediately if you have hives along with any of the following symptoms:

- trouble swallowing
- dizziness or loss of consciousness
- swelling of tongue
- swelling in or around mouth
- trouble speaking
- drooling
- wheezing or problems breathing

These symptoms may be signs of anaphylactic shock. This condition can be life threatening if not treated by a health professional immediately. Symptoms of anaphylactic shock may occur when hives first appear or up to a few hours later.
Not a Substitute for Epinephrine. If your doctor has prescribed an epinephrine injector for "anaphylaxis" or severe allergy symptoms that could occur with your hives, never use this product as a substitute for the epinephrine injector. If you have been prescribed an epinephrine injector, you should carry it with you at all times.

Do not use

- to prevent hives from any known cause such as:
  - foods
  - insect stings
  - medicines
  - latex or rubber gloves

because this product will not stop hives from occurring. Avoiding the cause of your hives is the only way to prevent them. Hives can sometimes be serious. If you do not know the cause of your hives, see your doctor for a medical exam. Your doctor may be able to help you find a cause.

- if you have ever had an allergic reaction to this product or any of its ingredients or to an antihistamine containing hydroxyzine.

Ask a doctor before use if you have

- liver or kidney disease. Your doctor should determine if you need a different dose.
- hives that are an unusual color, look bruised or blistered
- hives that do not itch

Ask a doctor or pharmacist before use if you are

taking tranquilizers or sedatives.

When using this product

- drowsiness may occur
- avoid alcoholic drinks
- alcohol, sedatives, and tranquilizers may increase drowsiness
- be careful when driving a motor vehicle or operating machinery

Stop use and ask a doctor if

- an allergic reaction to this product occurs. Seek medical help right away.
- symptoms do not improve after 3 days of treatment.
- the hives have lasted more than 6 weeks.

If pregnant or breast-feeding:

- if breast-feeding: not recommended
- if pregnant: ask a health professional before use.

Keep out of reach of children.

In case of overdose, get medical help or contact a Poison Control Center right away. [1-800-222-1222]

Directions

For 5 mg:

adults and children 6 years and over | 1 to 2 tablets once daily depending upon severity of symptoms; do not take more than 2 tablets in 24 hours
adults 65 years and over | 1 tablet once a day; do not take more than 1 tablet in 24 hours.
children under 6 years of age | ask a doctor
consumers with liver or kidney disease | ask a doctor

For 10 mg:

adults and children 6 years and over | one 10 mg tablet once daily; do not take more than one 10 mg tablet in 24 hours. A 5 mg product may be appropriate for less severe symptoms.
adults 65 years and over | ask a doctor
children under 6 years of age | ask a doctor
consumers with liver or kidney disease | ask a doctor

Other information

- store between 20° to 25°C (68° to 77°F)
- TAMPER EVIDENT: DO NOT USE IF SEAL OVER BOTTLE OPENING IS BROKEN OR MISSING.

Inactive ingredients

colloidal silicon dioxide, croscarmellose sodium, hypromellose, lactose monohydrate, magnesium stearate, microcrystalline cellulose, polyethylene glycol, titanium dioxide

Questions?

call 1-855-274-4122
Important: Read all product information before using. Keep this carton for important information.
Distributed by:
AUROHEALTH LLC
279 Princeton-Hightstown Road
East Windsor, NJ 08520

PACKAGE LABEL-PRINCIPAL DISPLAY PANEL - 5 mg (30's Tablet Container Carton Label)

AUROHEALTH
NDC 58602-446-09
*Compare to the active
ingredient of Zyrtec®
HIVES RELIEF
Cetirizine Hydrochloride Tablets USP
5 mg
Antihistamine
Original Prescription Strength
HIVES RELIEF
24 Hour relief Reduces
Hives
30
Tablets Reduces Itching
5 mg each Due to Hives

PACKAGE LABEL-PRINCIPAL DISPLAY PANEL - 5 mg (10 x 10 Blister Carton Label)

AUROHEALTH
NDC 58602-446-21
*Compare to the active
ingredient of Zyrtec®
HIVES RELIEF
Cetirizine Hydrochloride Tablets USP
5 mg
Antihistamine
Original Prescription Strength
HIVES RELIEF
24 Hour relief Reduces
Hives
100
(10x10's)
Unit dose Tablets Reduces Itching
5 mg each Due to Hives

PACKAGE LABEL-PRINCIPAL DISPLAY PANEL - 10 mg (30's Tablet Container Carton Label)

AUROHEALTH
NDC 58602-447-09
*Compare to the active
ingredient of Zyrtec®
HIVES RELIEF
Cetirizine Hydrochloride Tablets USP 10 mg
Antihistamine
Original Prescription Strength
HIVES RELIEF
24 Hour relief Reduces
Hives
30
Tablets Reduces Itching
10 mg each Actual Size Due to Hives

PACKAGE LABEL-PRINCIPAL DISPLAY PANEL - 10 mg (10 x 10 Blister Carton Label)

AUROHEALTH
NDC 58602-447-21
*Compare to the active
ingredient of Zyrtec®
HIVES RELIEF
Cetirizine Hydrochloride Tablets USP 10 mg
Antihistamine
Original Prescription Strength
HIVES RELIEF
24 Hour relief Reduces
Hives
100 Tablets
(10x10 Unit-dose) Reduces Itching
10 mg each Actual Size Due to Hives